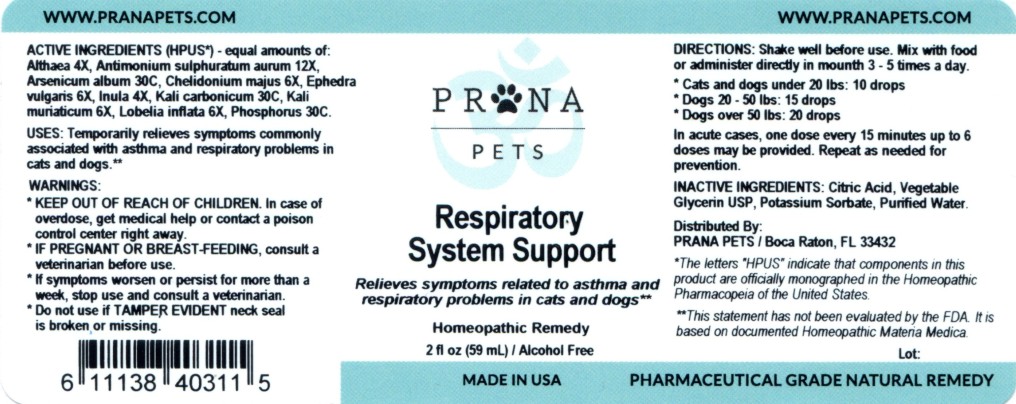 DRUG LABEL: Respiratory System Support
NDC: 86066-003 | Form: LIQUID
Manufacturer: Surefreight Global LLC, DBA PRANAPETS
Category: homeopathic | Type: OTC ANIMAL DRUG LABEL
Date: 20171122

ACTIVE INGREDIENTS: ALTHAEA OFFICINALIS ROOT 4 [hp_X]/59 mL; ANTIMONY PENTASULFIDE 12 [hp_X]/59 mL; ARSENIC TRIOXIDE 30 [hp_C]/59 mL; CHELIDONIUM MAJUS 6 [hp_X]/59 mL; EPHEDRA DISTACHYA FLOWERING TWIG 6 [hp_X]/59 mL; INULA HELENIUM ROOT 4 [hp_X]/59 mL; POTASSIUM CARBONATE 30 [hp_C]/59 mL; POTASSIUM CHLORIDE 6 [hp_X]/59 mL; LOBELIA INFLATA 6 [hp_X]/59 mL; PHOSPHORUS 30 [hp_C]/59 mL
INACTIVE INGREDIENTS: WATER; GLYCERIN; CITRIC ACID MONOHYDRATE; POTASSIUM SORBATE

Respiratory System Support

ACTIVE INGREDIENT

ACTIVE INGREDIENTS (HPUS*) - equal amounts of: Althaea 4X, Antimonium sulphuratum aurum 12X, Arsenicum album 30C, Chelidonium majus 6X, Ephedra vulgaris 6X, Inula 4X, Kali carbonicum 30C, Kali muriaticum 6X, Lobelia inflata 6X, Phosphorus 30C.

OTHER SAFETY INFORMATION

* The letters "HPUS" indicate that components in this product are officially monographed in the Homeopathic Pharmacopeia of the United States.

INDICATIONS AND USAGE

USES: Temporarily relieves symptoms commonly associated with asthma and respiratory problems in cats and dogs.**

OTHER SAFETY INFORMATION

** This statement has not been evaluated by the FDA. It is based on documented Homeopathic Materia Medica.

WARNINGS:

- KEEP OUT OF REACH OF CHILDREN. In case of overdose, get medical help or contact a poison control center right away.
- IF PREGNANT OR BREAST-FEEDING, consult a veterinarian before use.
- If symptoms worsen or persist for more than a week, stop use and consult a veterinarian.
- Do not use if TAMPER EVIDENT neck seal is broken or missing.

DOSAGE AND ADMINISTRATION

DIRECTIONS: Shake well before use. Mix with food or administer directly in mouth 3 - 5 times a day.

- Cats and dogs under 20 lbs: 10 drops
- Dogs 20 - 50 lbs: 15 drops
- Dogs over 50 lbs: 20 drops

In acute cases, one dose every 15 minutes up to 6 doses may be provided. Repeat as needed for prevention.

INACTIVE INGREDIENT

INACTIVE INGREDIENTS: Citric Acid, Vegetable Glycerin USP, Potassium Sorbate, Purified Water.

QUESTIONS

Distributed by:

PRANA PETS / Boca Raton, FL 33432

www.pranapets.com

PACKAGE LABEL

PRANA PETS

Respiratory System Support

Relieves symptoms related to asthma and respiratory problems in cats and dogs**

Homeopathic Remedy

2 fl oz (59 mL) / Alcohol Free

Made in USA

Pharmaceutical Grade Natural Remedy